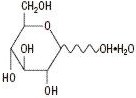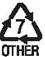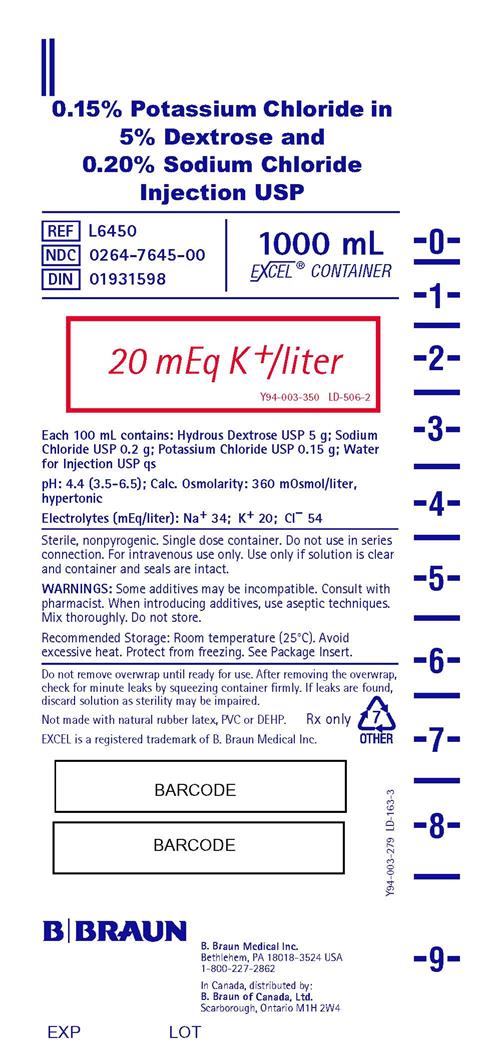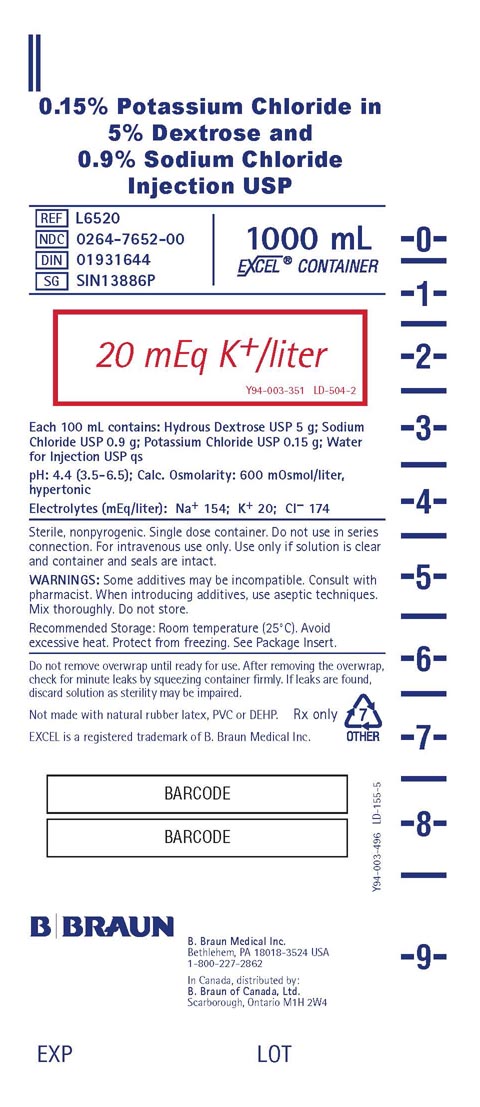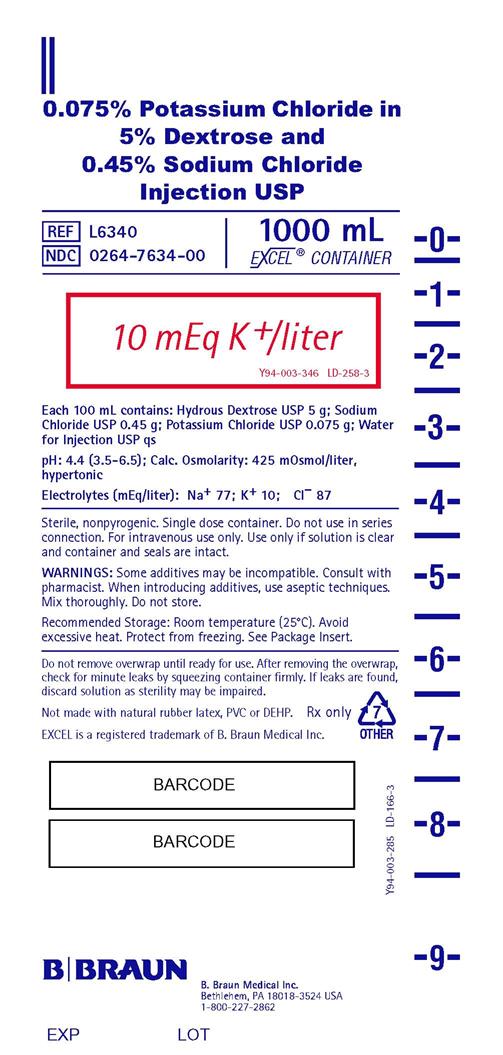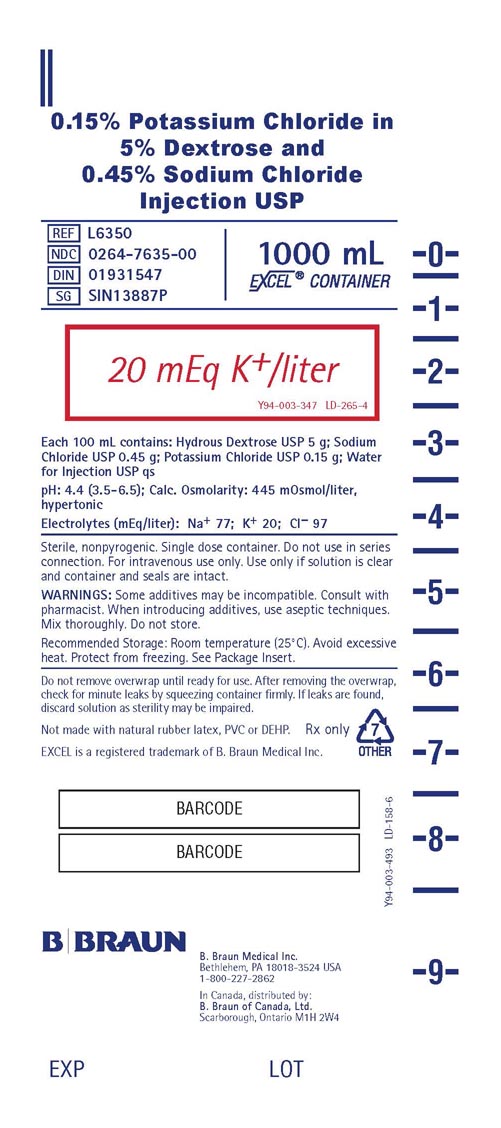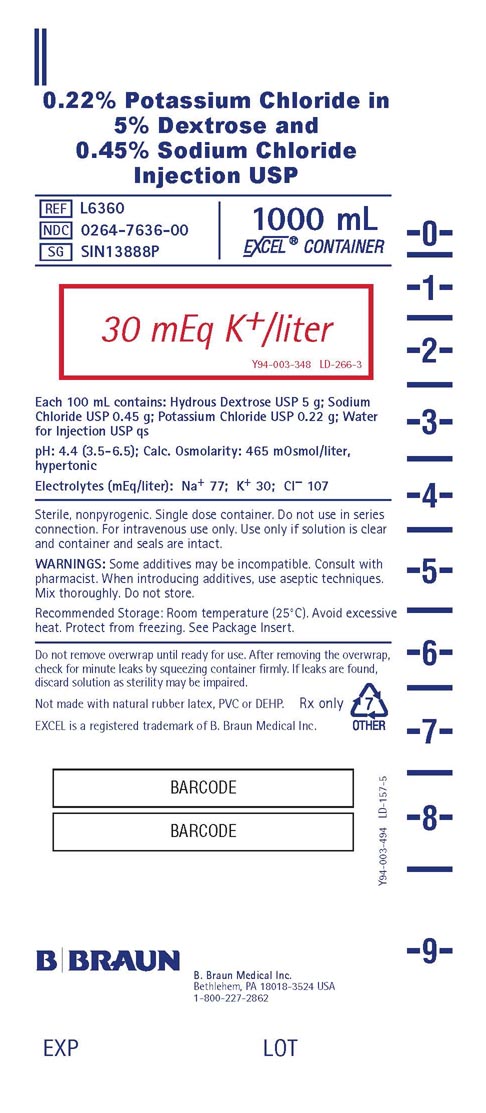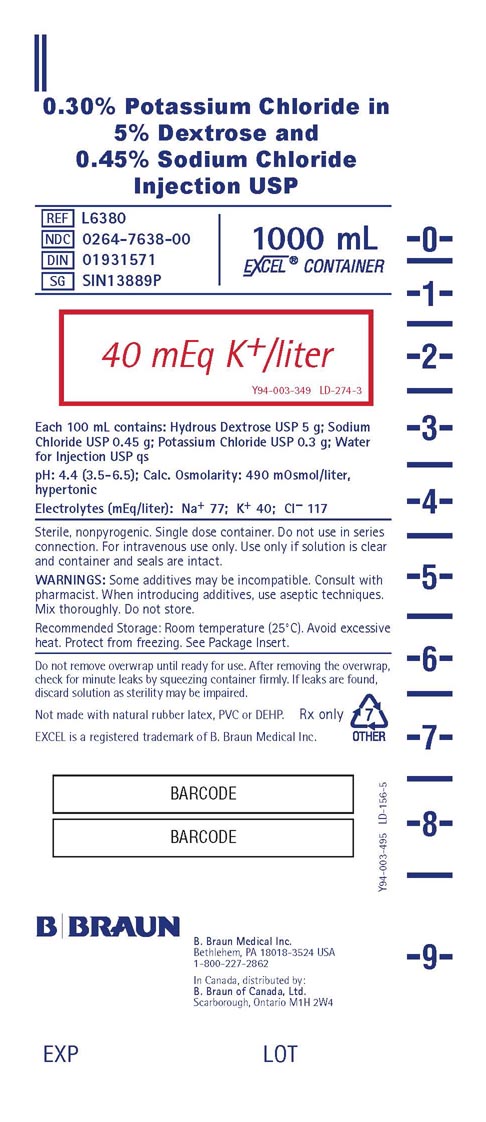 DRUG LABEL: Potassium Chloride in Dextrose and Sodium Chloride
NDC: 0264-7645 | Form: INJECTION
Manufacturer: B. Braun Medical Inc.
Category: prescription | Type: HUMAN PRESCRIPTION DRUG LABEL
Date: 20240326

ACTIVE INGREDIENTS: DEXTROSE, UNSPECIFIED FORM 5 g/100 mL; SODIUM CHLORIDE 0.2 g/100 mL; POTASSIUM CHLORIDE 0.15 g/100 mL
INACTIVE INGREDIENTS: WATER

Potassium Chloride in Dextrose and Sodium Chloride Injections USP

DESCRIPTION

(See chart below for quantitative information.)

Potassium Chloride in Dextrose and Sodium Chloride Injections USP are sterile, nonpyrogenic and contain no bacteriostatic or antimicrobial agents. These products are intended for intravenous administration.

The formulas of the active ingredients are:

Ingredients | Molecular Formula | Molecular Weight
Sodium Chloride USP Potassium Chloride USP | NaCl KCl | 58.44 74.55
Hydrous Dextrose USP |  | 198.17

Not made with natural rubber latex, PVC or DEHP.

The plastic container is made from a multilayered film specifically developed for parenteral drugs. It contains no plasticizers and exhibits virtually no leachables. The solution contact layer is a rubberized copolymer of ethylene and propylene. The container is nontoxic and biologically inert. The container-solution unit is a closed system and is not dependent upon entry of external air during administration. The container is overwrapped to provide protection from the physical environment and to provide an additional moisture barrier when necessary.

Composition – Each 100 mL contains:
Solution | Hydrous Dextrose USP | Sodium Chloride USP | Potassium Chloride USP | Concentration of Electrolytes (mEq/liter) |  |  | Calories per liter | Calculated Osmolarity mOsmol/liter | pH
Solution | Hydrous Dextrose USP | Sodium Chloride USP | Potassium Chloride USP | Sodium | Potassium | Chloride | Calories per liter | Calculated Osmolarity mOsmol/liter | pH
0.15% Potassium Chloride in 5% Dextrose and 0.20% Sodium Chloride Injection USP | 5 g | 0.2 g | 0.15 g | Sodium | Potassium | Chloride | 34 | 20 | 54 | 170 | 360 | 4.4 (3.5–6.5)
0.075% Potassium Chloride in 5% Dextrose and 0.45% Sodium Chloride Injection USP | 5 g | 0.45 g | 0.075 g | 77 | 10 | 87 | 170 | 425 | 4.4 (3.5–6.5)
0.15% Potassium Chloride in 5% Dextrose and 0.45% Sodium Chloride Injection USP | 5 g | 0.45 g | 0.15 g | 77 | 20 | 97 | 170 | 445 | 4.4 (3.5–6.5)
0.22% Potassium Chloride in 5% Dextrose and 0.45% Sodium Chloride Injection USP | 5 g | 0.45 g | 0.22 g | 77 | 30 | 107 | 170 | 465 | 4.4 (3.5–6.5)
0.30% Potassium Chloride in 5% Dextrose and 0.45% Sodium Chloride Injection USP | 5 g | 0.45 g | 0.3 g | 77 | 40 | 117 | 170 | 490 | 4.4 (3.5–6.5)
0.15% Potassium Chloride in 5% Dextrose and 0.9% Sodium Chloride Injection USP | 5 g | 0.9 g | 0.15 g | 154 | 20 | 174 | 170 | 600 | 4.4 (3.5–6.5)
Water for Injection USP qs

Addition of medication should be accomplished using complete aseptic technique.

The closure system has two ports; the one for the administration set has a tamper evident plastic protector and the other is a medication addition site. Refer to the Directions for Use of the container.

CLINICAL PHARMACOLOGY

These intravenous solutions provide electrolytes and calories, and are a source of water for hydration. They are capable of inducing diuresis depending on the clinical condition of the patient.

Sodium, the major cation of the extracellular fluid, functions primarily in the control of water distribution, fluid balance, and osmotic pressure of body fluids. Sodium is also associated with chloride and bicarbonate in the regulation of the acid-base equilibrium of body fluid.

Potassium, the principal cation of intracellular fluid, participates in carbohydrate utilization and protein synthesis, and is critical in the regulation of nerve conduction and muscle contraction, particularly in the heart.

Chloride, the major extracellular anion, closely follows the metabolism of sodium, and changes in the acid-base balance of the body are reflected by changes in the chloride concentration.

Dextrose provides a source of calories. Dextrose is readily metabolized, may decrease losses of body protein and nitrogen, promotes glycogen deposition and decreases or prevents ketosis if sufficient doses are provided.

INDICATIONS AND USAGE

These intravenous solutions are indicated for use in adults and pediatric patients as sources of electrolytes, calories and water for hydration.

CONTRAINDICATIONS

These solutions are contraindicated where the administration of sodium, potassium or chloride could be clinically detrimental.

Solutions containing dextrose may be contraindicated in patients with hypersensitivity to corn products.

WARNINGS

The administration of intravenous solutions can cause fluid and/or solute overload resulting in dilution of serum electrolyte concentrations, overhydration, congested states or pulmonary edema. The risk of dilutional states is inversely proportional to the electrolyte concentration. The risk of solute overload causing congested states with peripheral and pulmonary edema is directly proportional to the electrolyte concentration.

Solutions containing sodium ions should be used with great care, if at all, in patients with congestive heart failure, severe renal insufficiency, and in clinical states in which there is sodium retention with edema.

In patients with diminished renal function, administration of solutions containing sodium or potassium ions may result in sodium or potassium retention.

Solutions containing potassium ions should be used with great care, if at all, in patients with hyperkalemia, severe renal failure, and in conditions in which potassium retention is present.

To avoid life-threatening hyperkalemia, do not administer Potassium Chloride in Dextrose and Sodium Chloride Injections USP as an intravenous push (i.e., intravenous injection manually with a syringe connected to the intravenous access, without a quantitative infusion device).

PRECAUTIONS

General

These solutions should be used with care in patients with hypervolemia, renal insufficiency, urinary tract obstruction, or impending or frank cardiac decompensation.

Extraordinary electrolyte losses such as may occur during protracted nasogastric suction, vomiting, diarrhea or gastrointestinal fistula drainage may necessitate additional electrolyte supplementation.

Additional essential electrolytes, minerals and vitamins should be supplied as needed.

Sodium-containing solutions should be administered with caution to patients receiving corticosteroids or corticotropin, or to other salt-retaining patients.

Care should be exercised in administering solutions containing sodium or potassium to patients with renal or cardiovascular insufficiency, with or without congestive heart failure, particularly if they are postoperative or elderly.

Potassium therapy should be guided primarily by serial electrocardiograms, especially in patients receiving digitalis. Serum potassium levels are not necessarily indicative of tissue potassium levels. Solutions containing potassium should be used with caution in the presence of cardiac disease, particularly when accompanied by renal disease.

Solutions containing dextrose should be used with caution in patients with overt or known subclinical diabetes mellitus, or carbohydrate intolerance for any reason.

To minimize the risk of possible incompatibilities arising from mixing any of these solutions with other additives that may be prescribed, the final infusate should be inspected for cloudiness or precipitation immediately after mixing, prior to administration, and periodically during administration.

Do not use plastic containers in series connection.

If administration is controlled by a pumping device, care must be taken to discontinue pumping action before the container runs dry or air embolism may result. If administration is not controlled by a pumping device, refrain from applying excessive pressure (>300mmHg) causing distortion to the container such as wringing or twisting. Such handling could result in breakage of the container.

These solutions are intended for intravenous administration using sterile equipment. Use only if solution is clear and container and seals are intact.

Laboratory Tests

Clinical evaluation and periodic laboratory determinations are necessary to monitor changes in fluid balance, electrolyte concentrations, and acid-base balance during prolonged parenteral therapy or whenever the condition of the patient warrants such evaluation. Significant deviations from normal concentrations may require tailoring of the electrolyte pattern, in these or alternative solutions.

Carcinogenesis, Mutagenesis, Impairment of Fertility

Studies with Potassium Chloride in Dextrose and Sodium Chloride Injections USP have not been performed to evaluate carcinogenic potential, mutagenic potential, or effects on fertility.

Pregnancy

Teratogenic Effects

Animal reproduction studies have not been conducted with Potassium Chloride in Dextrose and Sodium Chloride Injections USP. It is also not known whether Potassium Chloride in Dextrose and Sodium Chloride Injections USP can cause fetal harm when administered to a pregnant woman or can affect reproduction capacity. Potassium Chloride in Dextrose and Sodium Chloride Injections USP should be given to a pregnant woman only if clearly needed.

Labor and Delivery

The effects of Potassium Chloride in Dextrose and Sodium Chloride Injections USP on the duration of labor or delivery, on the possibility that forceps delivery or other intervention or resuscitation of the newborn will be necessary, and on the later growth, development, and functional maturation of the child are unknown.

As reported in the literature, potassium containing solutions have been administered during labor and delivery. Caution should be exercised, and the fluid balance, glucose and electrolyte concentrations, and acid-base balance, of both mother and fetus should be evaluated periodically or whenever warranted by the condition of the patient or fetus.

Nursing Mothers

It is not known whether these drugs are excreted in human milk. Because many drugs are excreted in human milk, caution should be exercised when Potassium Chloride in Dextrose and Sodium Chloride Injections USP are administered to a nursing woman.

Pediatric Use

Safety and effectiveness of Potassium Chloride in Dextrose and Sodium Chloride Injections USP in pediatric patients have not been established by adequate and well-controlled studies. However, as referenced in the medical literature, potassium chloride injection has been used to treat pediatric patients with potassium deficiency when oral replacement therapy is not feasible.

For patients receiving potassium supplement at greater than maintenance rates, frequent monitoring of serum potassium levels and serial EKGs are recommended.

Dextrose is safe and effective for the stated indications in pediatric patients (see INDICATIONS AND USAGE). As reported in the literature, the dosage selection and constant infusion rate of intravenous dextrose must be selected with caution in pediatric patients, particularly neonates and low birth weight infants, because of the increased risk of hyperglycemia/hypoglycemia. Frequent monitoring of serum glucose concentrations is required when dextrose is prescribed to pediatric patients, particularly neonates and low birth weight infants.

In neonates or in very small infants even small volumes of fluid may affect fluid and electrolyte balance. Care must be exercised in treatment of neonates, especially pre-term neonates, whose renal function may be immature and whose ability to excrete fluid and solute loads may be limited. Fluid intake, urine output, and serum electrolytes should be monitored closely.

See WARNINGS and DOSAGE AND ADMINISTRATION.

Geriatric Use

Clinical studies of Potassium Chloride in Dextrose and Sodium Chloride Injections USP did not include sufficient numbers of subjects aged 65 and over to determine whether they respond differently from younger subjects. Other reported clinical experience has not identified differences in responses between elderly and younger patients.

In general, dose selection for an elderly patient should be cautious, usually starting at the low end of the dosing range, reflecting the greater frequency of decreased hepatic, renal, or cardiac function, and of concomitant disease or other drug therapy.

These drugs are known to be substantially excreted by the kidney, and the risk of toxic reactions to these drugs may be greater in patients with impaired renal function. Because elderly patients are more likely to have decreased renal function, care should be taken in dose selection, and it may be useful to monitor renal function.

See WARNINGS.

ADVERSE REACTIONS

Reactions which may occur because of the solution or the technique of administration include febrile response, infection at the site of injection, venous thrombosis or phlebitis extending from the site of injection, extravasation and hypervolemia.

Too rapid infusion of hypertonic solutions may cause local pain and venous irritation. Rate of administration should be adjusted according to tolerance. Use of the largest peripheral vein and a small bore needle is recommended. (See DOSAGE AND ADMINISTRATION.)

Symptoms may result from an excess or deficit of one or more of the ions present in the solution; therefore, frequent monitoring of electrolyte levels is essential.

Hypernatremia may be associated with edema and exacerbation of congestive heart failure due to the retention of water, resulting in an expanded extracellular fluid volume.

Reactions reported with the use of potassium-containing solutions include nausea, vomiting, abdominal pain and diarrhea. The signs and symptoms of potassium intoxication include paresthesias of the extremities, areflexia, muscular or respiratory paralysis, mental confusion, weakness, hypotension, cardiac arrhythmias, heart block, electrocardiographic abnormalities and cardiac arrest.

Potassium deficits result in disruption of neuromuscular function, and intestinal ileus and dilatation.

If infused in large amounts, chloride ions may cause a loss of bicarbonate ions, resulting in an acidifying effect.

The physician should also be alert to the possibility of adverse reaction to drug additives. Prescribing information for drug additives to be administered in this manner should be consulted.

If an adverse reaction does occur, discontinue the infusion, evaluate the patient, institute appropriate therapeutic countermeasures and save the remainder of the fluid for examination if deemed necessary.

OVERDOSAGE

In the event of fluid overload during parenteral therapy, reevaluate the patient's condition, and institute appropriate corrective treatment.

In the event of overdosage with potassium-containing solutions, discontinue the infusion immediately and institute corrective therapy to reduce serum potassium levels.

Treatment of hyperkalemia includes the following:

1. Dextrose Injection USP, 10% or 25%, containing 10 units of crystalline insulin per 20 grams of dextrose administered intravenously, 300 to 500 mL per hour.
2. Absorption and exchange of potassium using sodium or ammonium cycle cation exchange resin, orally and as retention enema.
3. Hemodialysis and peritoneal dialysis. The use of potassium-containing foods or medications must be eliminated. However, in cases of digitalization, too rapid a lowering of plasma potassium concentration can cause digitalis toxicity.

DOSAGE AND ADMINISTRATION

These solutions are for intravenous use only.

Dosage is to be directed by a physician and is dependent upon age, weight, clinical condition of the patient and laboratory determinations. Frequent laboratory determinations and clinical evaluation are essential to monitor changes in blood glucose and electrolyte concentrations, and fluid and electrolyte balance during prolonged parenteral therapy.

When a hypertonic solution is to be administered peripherally, it should be slowly infused through a small bore needle, placed well within the lumen of a large vein to minimize venous irritation. Carefully avoid infiltration.

Usually, up to 40 mEq of potassium per liter daily is sufficient to replace normal loss in adults. Typical infusion rates should not exceed 10 mEq per hour or 120 mEq per day. Pediatric patients may require 2 to 3 mEq per kg of body weight daily. See WARNINGS and PRECAUTIONS for pediatric use.

Fluid administration should be based on calculated maintenance or replacement fluid requirements for each patient.

Dextrose may be administered to normal individuals at a rate of 0.5 g/kg/hour without producing glycosuria. At the maximum infusion rate of 0.8 g/kg/hour, approximately 95% of the dextrose is retained.

Potassium Chloride in Dextrose and Sodium Chloride Injections USP should not be administered simultaneously with blood through the same administration set because of the possibility of pseudoagglutination or hemolysis.

Some additives may be incompatible. Consult with pharmacist. When introducing additives, use aseptic techniques. Mix thoroughly. Do not store.

Parenteral drug products should be inspected visually for particulate matter and discoloration prior to administration, whenever solution and container permit.

HOW SUPPLIED

Potassium Chloride in Dextrose and Sodium Chloride Injections USP are supplied in EXCEL® Containers. The 1000 mL containers are packaged 12 per case.

Canada DIN | NDC | REF | Size
0.15% Potassium Chloride in 5% Dextrose and 0.20% Sodium Chloride Injection USP (20 mEq K^+/liter)
01931598 | 0264-7645-00 | L6450 | 1000 mL
0.075% Potassium Chloride in 5% Dextrose and 0.45% Sodium Chloride Injection USP (10 mEq K^+/liter)
 | 0264-7634-00 | L6340 | 1000 mL
0.15% Potassium Chloride in 5% Dextrose and 0.45% Sodium Chloride Injection USP (20 mEq K^+/liter)
01931547 | 0264-7635-00 | L6350 | 1000 mL
0.22% Potassium Chloride in 5% Dextrose and 0.45% Sodium Chloride Injection USP (30 mEq K^+/liter)
 | 0264-7636-00 | L6360 | 1000 mL
0.30% Potassium Chloride in 5% Dextrose and 0.45% Sodium Chloride Injection USP (40 mEq K^+/liter)
01931571 | 0264-7638-00 | L6380 | 1000 mL
0.15% Potassium Chloride in 5% Dextrose and 0.9% Sodium Chloride Injection USP (20 mEq K^+/liter)
01931644 | 0264-7652-00 | L6520 | 1000 mL

STORAGE AND HANDLING

Exposure of pharmaceutical products to heat should be minimized. Avoid excessive heat. Protect from freezing. It is recommended that the product be stored at room temperature (25°C).

Rx only

Revised: June 2023

EXCEL is a registered trademark of B. Braun Medical Inc.

Directions for Use of EXCEL Container

Caution: Do not use plastic containers in series connection.

To Open

Tear overwrap down at notch and remove solution container.
Check for minute leaks by squeezing solution container firmly.
If leaks are found, discard solution as sterility may be impaired.
If supplemental medication is desired, follow directions below before preparing for administration.

NOTE: Before use, perform the following checks:

- Inspect each container. Read the label. Ensure solution is the one ordered and is within the expiration date.
- Invert container and carefully inspect the solution in good light for cloudiness, haze, or particulate matter. Any container which is suspect should not be used.
- Use only if solution is clear and container and seals are intact.

Preparation for Administration

1. Remove plastic protector from sterile set port at bottom of container.
2. Attach administration set. Refer to complete directions accompanying set.

To Add Medication

Warning: Some additives may be incompatible.

To Add Medication Before Solution Administration

1. Prepare medication site.
2. Using syringe with 18–22 gauge needle, puncture medication port and inner diaphragm and inject.
3. Squeeze and tap ports while ports are upright and mix solution and medication thoroughly.

To Add Medication During Solution Administration

1. Close clamp on the set.
2. Prepare medication site.
3. Using syringe with 18–22 gauge needle of appropriate length (at least 5/8 inch), puncture resealable medication port and inner diaphragm and inject.
4. Remove container from IV pole and/or turn to an upright position.
5. Evacuate both ports by tapping and squeezing them while container is in the upright position.
6. Mix solution and medication thoroughly.
7. Return container to in use position and continue administration.

B. Braun Medical Inc.
Bethlehem, PA 18018-3524 USA
1-800-227-2862

In Canada, distributed by:
B. Braun of Canada, Ltd.
Scarborough, Ontario M1H 2W4

Y36-003-066 LD-196-5

PRINCIPAL DISPLAY PANEL - 1000 mL Container Label

0.075% Potassium Chloride in
5% Dextrose and
0.45% Sodium Chloride
Injection USP

REF L6340
NDC 0264-7634-00

1000 mL
EXCEL® CONTAINER

10 mEq K^+/liter
Y94-003-346 LD-258-3

Each 100 mL contains: Hydrous Dextrose USP 5 g; Sodium
Chloride USP 0.45 g; Potassium Chloride USP 0.075 g; Water
for Injection USP qs

pH: 4.4 (3.5-6.5); Calc. Osmolarity: 425 mOsmol/liter,
hypertonic

Electrolytes (mEq/liter): Na^+ 77; K^+ 10; Cl^– 87

Sterile, nonpyrogenic. Single dose container. Do not use in series
connection. For intravenous use only. Use only if solution is clear
and container and seals are intact.

WARNINGS: Some additives may be incompatible. Consult with
pharmacist. When introducing additives, use aseptic techniques.
Mix thoroughly. Do not store.

Recommended Storage: Room temperature (25°C). Avoid
excessive heat. Protect from freezing. See Package Insert.

Do not remove overwrap until ready for use. After removing the overwrap,
check for minute leaks by squeezing container firmly. If leaks are found,
discard solution as sterility may be impaired.

Not made with natural rubber latex, PVC or DEHP.

Rx only
EXCEL is a registered trademark of B. Braun Medical Inc.

B. Braun Medical Inc.
Bethlehem, PA 18018-3524 USA
1-800-227-2862

Y94-003-285
LD-166-3

EXP LOT

PRINCIPAL DISPLAY PANEL - 1000 mL Container Label

0.15% Potassium Chloride in
5% Dextrose and
0.45% Sodium Chloride
Injection USP

REF L6350
NDC 0264-7635-00
DIN 01931547
SG SIN13887P

1000 mL
EXCEL® CONTAINER

20 mEq K^+/liter
Y94-003-347 LD-265-4

Each 100 mL contains: Hydrous Dextrose USP 5 g; Sodium
Chloride USP 0.45 g; Potassium Chloride USP 0.15 g; Water
for Injection USP qs

pH: 4.4 (3.5-6.5); Calc. Osmolarity: 445 mOsmol/liter,
hypertonic

Electrolytes (mEq/liter): Na^+ 77; K^+ 20; Cl^– 97

Sterile, nonpyrogenic. Single dose container. Do not use in series
connection. For intravenous use only. Use only if solution is clear
and container and seals are intact.

WARNINGS: Some additives may be incompatible. Consult with
pharmacist. When introducing additives, use aseptic techniques.
Mix thoroughly. Do not store.

Recommended Storage: Room temperature (25°C). Avoid excessive
heat. Protect from freezing. See Package Insert.

Do not remove overwrap until ready for use. After removing the overwrap,
check for minute leaks by squeezing container firmly. If leaks are found,
discard solution as sterility may be impaired.

Not made with natural rubber latex, PVC or DEHP.

Rx only

EXCEL is a registered trademark of B. Braun Medical Inc.

B. Braun Medical Inc.
Bethlehem, PA 18018-3524 USA
1-800-227-2862

In Canada, distributed by:
B. Braun of Canada, Ltd.
Scarborough, Ontario M1H 2W4

Y94-003-493
LD-158-6

EXP LOT

Y94-003-493

PRINCIPAL DISPLAY PANEL - 1000 mL Container Label

0.22% Potassium Chloride in
5% Dextrose and
0.45% Sodium Chloride
Injection USP

REF L6360
NDC 0264-7636-00
SG SIN13888P

1000 mL
EXCEL® CONTAINER

30 mEq K^+/liter
Y94-003-348 LD-266-3

Each 100 mL contains: Hydrous Dextrose USP 5 g; Sodium
Chloride USP 0.45 g; Potassium Chloride USP 0.22 g; Water
for Injection USP qs

pH: 4.4 (3.5-6.5); Calc. Osmolarity: 465 mOsmol/liter,
hypertonic

Electrolytes (mEq/liter): Na^+ 77; K^+ 30; Cl^– 107

Sterile, nonpyrogenic. Single dose container. Do not use in series
connection. For intravenous use only. Use only if solution is clear
and container and seals are intact.

WARNINGS: Some additives may be incompatible. Consult with
pharmacist. When introducing additives, use aseptic techniques.
Mix thoroughly. Do not store.

Recommended Storage: Room temperature (25°C). Avoid excessive
heat. Protect from freezing. See Package Insert.

Do not remove overwrap until ready for use. After removing the overwrap,
check for minute leaks by squeezing container firmly. If leaks are found,
discard solution as sterility may be impaired.

Not made with natural rubber latex, PVC or DEHP.

Rx only

EXCEL is a registered trademark of B. Braun Medical Inc.

B. Braun Medical Inc.
Bethlehem, PA 18018-3524 USA
1-800-227-2862

Y94-003-494
LD-157-5

EXP LOT

Y94-003-494

PRINCIPAL DISPLAY PANEL - 1000 mL Container Label

0.30% Potassium Chloride in
5% Dextrose and
0.45% Sodium Chloride
Injection USP

REF L6380
NDC 0264-7638-00
DIN 01931571
SG SIN13889P

1000 mL
EXCEL® CONTAINER

40 mEq K^+/liter
Y94-003-349 LD-274-3

Each 100 mL contains: Hydrous Dextrose USP 5 g; Sodium
Chloride USP 0.45 g; Potassium Chloride USP 0.3 g; Water
for Injection USP qs

pH: 4.4 (3.5-6.5); Calc. Osmolarity: 490 mOsmol/liter,
hypertonic

Electrolytes (mEq/liter): Na^+ 77; K^+ 40; Cl^– 117

Sterile, nonpyrogenic. Single dose container. Do not use in series
connection. For intravenous use only. Use only if solution is clear
and container and seals are intact.

WARNINGS: Some additives may be incompatible. Consult with
pharmacist. When introducing additives, use aseptic techniques.
Mix thoroughly. Do not store.

Recommended Storage: Room temperature (25°C). Avoid excessive
heat. Protect from freezing. See Package Insert.

Do not remove overwrap until ready for use. After removing the overwrap,
check for minute leaks by squeezing container firmly. If leaks are found,
discard solution as sterility may be impaired.

Not made with natural rubber latex, PVC or DEHP.

Rx only

EXCEL is a registered trademark of B. Braun Medical Inc.

B. Braun Medical Inc.
Bethlehem, PA 18018-3524 USA
1-800-227-2862

In Canada, distributed by:
B. Braun of Canada, Ltd.
Scarborough, Ontario M1H 2W4

Y94-003-495
LD-156-5

EXP LOT

Y94-003-495

PRINCIPAL DISPLAY PANEL - 1000 mL Container Label

0.15% Potassium Chloride in
5% Dextrose and
0.20% Sodium Chloride
Injection USP

REF L6450
NDC 0264-7645-00
DIN 01931598

1000 mL
EXCEL® CONTAINER

20 mEq K^+/liter
Y94-003-350 LD-506-2

Each 100 mL contains: Hydrous Dextrose USP 5 g; Sodium
Chloride USP 0.2 g; Potassium Chloride USP 0.15 g; Water
for Injection USP qs

pH: 4.4 (3.5-6.5); Calc. Osmolarity: 360 mOsmol/liter,
hypertonic

Electrolytes (mEq/liter): Na^+ 34; K^+ 20; Cl^– 54

Sterile, nonpyrogenic. Single dose container. Do not use in series
connection. For intravenous use only. Use only if solution is clear
and container and seals are intact.

WARNINGS: Some additives may be incompatible. Consult with
pharmacist. When introducing additives, use aseptic techniques.
Mix thoroughly. Do not store.

Recommended Storage: Room temperature (25°C). Avoid
excessive heat. Protect from freezing. See Package Insert.
Do not remove overwrap until ready for use. After removing the overwrap,
check for minute leaks by squeezing container firmly. If leaks are found,
discard solution as sterility may be impaired.

Not made with natural rubber latex, PVC or DEHP.

Rx only

EXCEL is a registered trademark of B. Braun Medical Inc.

B. Braun Medical Inc.
Bethlehem, PA 18018-3524 USA
1-800-227-2862

In Canada, distributed by:
B. Braun of Canada, Ltd.
Scarborough, Ontario M1H 2W4

Y94-003-279
LD-163-3

EXP LOT

PRINCIPAL DISPLAY PANEL - 1000 mL Container Label

0.15% Potassium Chloride in
5% Dextrose and
0.9% Sodium Chloride
Injection USP

REF L6520
NDC 0264-7652-00
DIN 01931644
SG SIN13886P

1000 mL
EXCEL® CONTAINER

20 mEq K^+/liter
Y94-003-351 LD-504-2

Each 100 mL contains: Hydrous Dextrose USP 5 g; Sodium
Chloride USP 0.9 g; Potassium Chloride USP 0.15 g; Water
for Injection USP qs

pH: 4.4 (3.5-6.5); Calc. Osmolarity: 600 mOsmol/liter,
hypertonic

Electrolytes (mEq/liter): Na^+ 154; K^+ 20; Cl^– 174

Sterile, nonpyrogenic. Single dose container. Do not use in series
connection. For intravenous use only. Use only if solution is clear
and container and seals are intact.

WARNINGS: Some additives may be incompatible. Consult with
pharmacist. When introducing additives, use aseptic techniques.
Mix thoroughly. Do not store.

Recommended Storage: Room temperature (25°C). Avoid
excessive heat. Protect from freezing. See Package Insert.

Do not remove overwrap until ready for use. After removing the overwrap,
check for minute leaks by squeezing container firmly. If leaks are found,
discard solution as sterility may be impaired.

Not made with natural rubber latex, PVC or DEHP.

Rx only

EXCEL is a registered trademark of B. Braun Medical Inc.

B. Braun Medical Inc.
Bethlehem, PA 18018-3524 USA
1-800-227-2862

In Canada, distributed by:
B. Braun of Canada, Ltd.
Scarborough, Ontario M1H 2W4

Y94-003-496
LD-155-5

EXP LOT

Y94-003-496